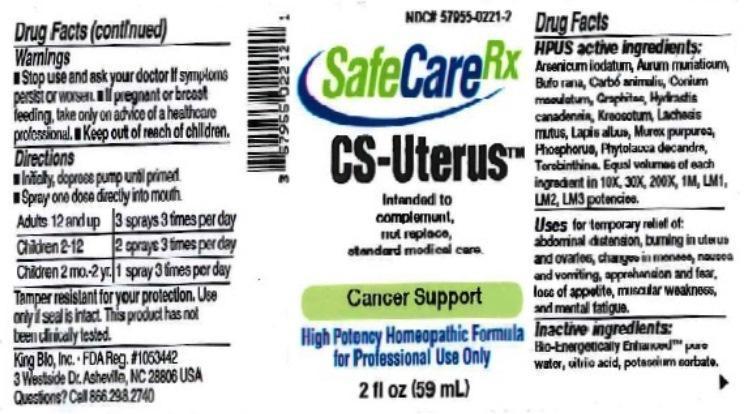 DRUG LABEL: CS Uterus
NDC: 57955-0221 | Form: LIQUID
Manufacturer: King Bio Inc.
Category: homeopathic | Type: HUMAN OTC DRUG LABEL
Date: 20150702

ACTIVE INGREDIENTS: ARSENIC TRIIODIDE 10 [hp_X]/59 mL; GOLD TRICHLORIDE 10 [hp_X]/59 mL; BUFO BUFO CUTANEOUS GLAND 10 [hp_X]/59 mL; CARBO ANIMALIS 10 [hp_X]/59 mL; CONIUM MACULATUM FLOWERING TOP 10 [hp_X]/59 mL; GRAPHITE 10 [hp_X]/59 mL; GOLDENSEAL 10 [hp_X]/59 mL; WOOD CREOSOTE 10 [hp_X]/59 mL; LACHESIS MUTA VENOM 10 [hp_X]/59 mL; CALCIUM HEXAFLUOROSILICATE 10 [hp_X]/59 mL; HEXAPLEX TRUNCULUS HYPOBRANCHIAL GLAND JUICE 10 [hp_X]/59 mL; PHOSPHORUS 10 [hp_X]/59 mL; PHYTOLACCA AMERICANA ROOT 10 [hp_X]/59 mL; TURPENTINE OIL 10 [hp_X]/59 mL
INACTIVE INGREDIENTS: WATER; ANHYDROUS CITRIC ACID; POTASSIUM SORBATE

CS Uterus™

ACTIVE INGREDIENT

Drug Facts__________________________________________________________________________________________________________

HPUS active ingredients: Arsenicum iodatum, Aurum muriaticum, Bufo rana, Carbo animalis, Conium maculatum, Graphites, Hydrastis canadensis, Kreosotum, Lachesis mutus, Lapis albus, Murex purpurea, Phosphorus, Phytolacca decandra, Terebinthina. Equal volumes of each ingredient in 10X, 30X, 200X, 1M, LM1, LM2, LM3 potencies.

INDICATIONS AND USAGE

Uses for temporary relief of: abdominal distension, burning in uterus and ovaries, changes in menses, nausea and vomiting, apprehension and fear, loss of appetite, muscular weakness, and mental fatigue.

Inactive Ingredients:

Bio-Energetically Enhanced™ pure water, citric acid and potassium sorbate.

Warnings

- Stop use and ask your doctor if symptoms persist or worsen.
- If pregnant or breast-feeding, take only on advice of a healthcare professional.

- Keep out of reach of children.

Directions

- Initially, depress pump until primed.
- Spray one dose directly into mouth.
- Adults 12 and up: 3 sprays 3 times per day.
- Children 2-12: 2 sprays 3 times per day.
- Children 2 mo.-2yr: 1 spray 3 times per day.

OTHER SAFETY INFORMATION

Tamper resistant for your protection. Use only if safety seal is intact. This product has not been clinically tested. Intended to complement, not replace, standard medical care.

PURPOSE

Uses for temporary relief of:

- abdominal distension
- burning in uterus and ovaries
- changes in menses
- nausea and vomiting
- apprehension and fear
- loss of appetite
- muscular weakness
- mental fatigue